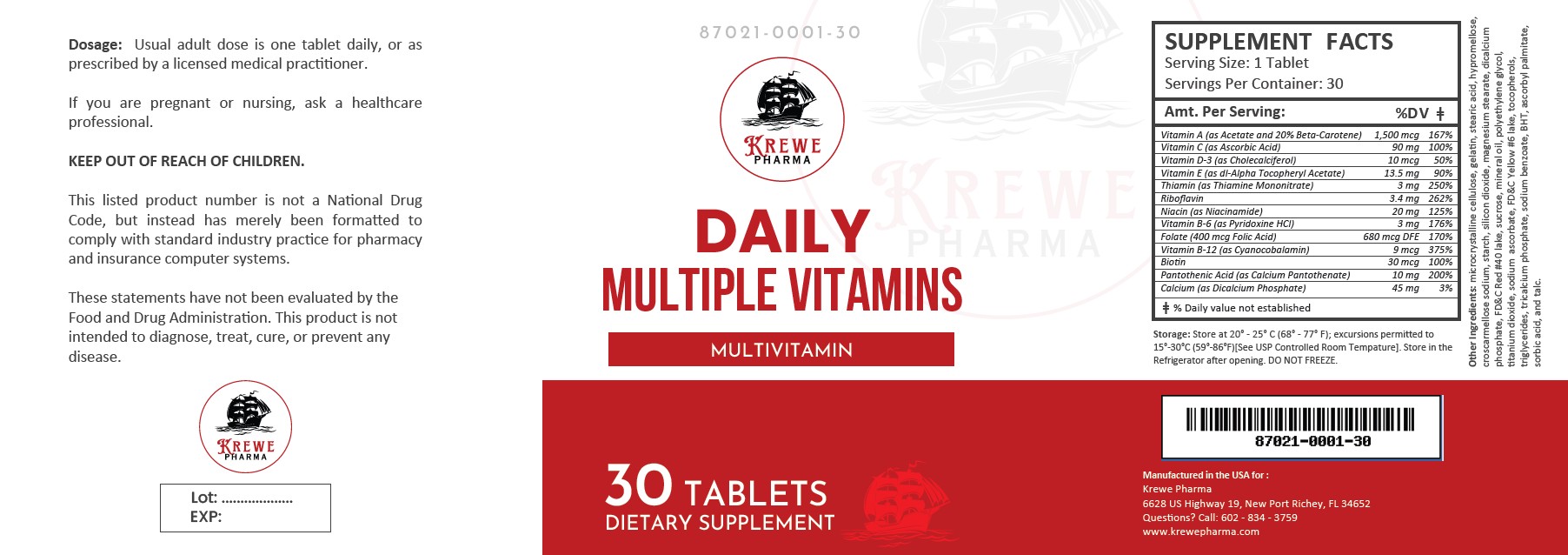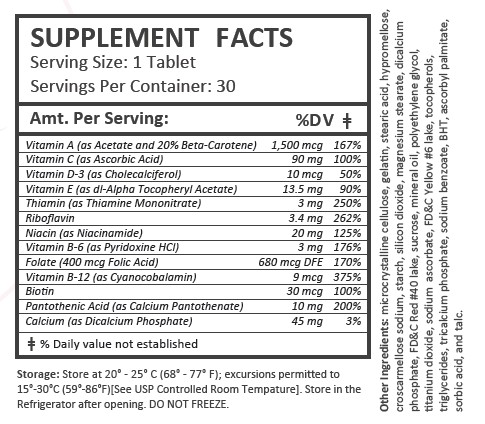 DRUG LABEL: Daily Multiple Vitamins
NDC: 87021-001 | Form: TABLET
Manufacturer: Krewe Pharma, LLC
Category: other | Type: Dietary Supplement
Date: 20251113

ACTIVE INGREDIENTS: ASCORBIC ACID 90 mg/1 1; BIOTIN 30 ug/1 1; CHOLECALCIFEROL 10 ug/1 1; CYANOCOBALAMIN 9 ug/1 1; FOLIC ACID 400 ug/1 1; NIACINAMIDE 20 mg/1 1; CALCIUM PANTOTHENATE 10 mg/1 1; PYRIDOXINE HYDROCHLORIDE 3 mg/1 1; VITAMIN A ACETATE 1500 ug/1 1; RIBOFLAVIN 3.4 mg/1 1; THIAMINE MONONITRATE 3 mg/1 1; .ALPHA.-TOCOPHEROL ACETATE, DL- 13.5 mg/1 1

Daily Multiple Vitamins

Health Claim Section:

Daily Multiple Vitamins

Other ingredients:
microcrystalline cellulose, gelatin, stearic acid, hypromellose, croscarmellose sodium, starch, silicon dioxide, magnesium stearate, dicalcium phosphate, FD&C Red #40 lake, sucrose, mineral oil, polyethylene glycol, titanium dioxide, sodium ascorbate, FD&C Yellow #6 lake, tocopherols, triglycerides, tricalcium phosphate, sodium benzoate, BHT, ascorbyl palmitate, sorbic acid, and talc.

Description:

Daily Multiple Vitamins are brown caplets dispensed in plastic bottles of 30 ct.

87021-0001-30

Reserved for Professional Recommendation

This listed product is not a National Drug Code, but instead has merely been formatted to comply with standard industry practice for pharmacy and insurance computer systems.

These statements have not been evaluated by the Food and Drug Administration. This product is not intended to diagnose, treat, cure or prevent any disease.

All prescriptions using this product shall be pursuant to state statutes as applicable. This is not an Orange Book product. This product may be administered only under a physician’s supervision. There are no implied or explicit claims on therapeutic equivalence.

Manufactured for:

Krewe Pharma

New Port Richey, FL 34652

Warnings and Precautions:

This product is contraindicated in patients with a known hypersensitivity to any of the ingredients.

As with any supplement, if you are pregnant, nursing, taking medication, or have a medical condition, ask a health professional before taking this product.

These statements have not been evaluated by the Food and Drug Administration. This product is not intended to diagnose, treat, cure, or prevent any disease.

Dosage and Administration:

Usual adult dose is one tablet daily, or as prescribed by a licensed medical practitioner.

Precautions:

CONTRAINDICATIONS
This product is contraindicated in patients with known hypersensitivity to any of the ingredients.

PRECAUTIONS
This product is contraindicated in patients with a known hypersensitivity to any of the ingredients.

ADVERSE REACTIONS
Allergic sensitizations have been reported following oral administration of folic acid. Consult your physician immediately if adverse side effects occur.

KEEP OUT OF THE REACH OF CHILDREN.

Storage:

Store at 20° to 25°C (68° to 77°F); excursions permitted to 15° to 30°C (59° to 86°F).